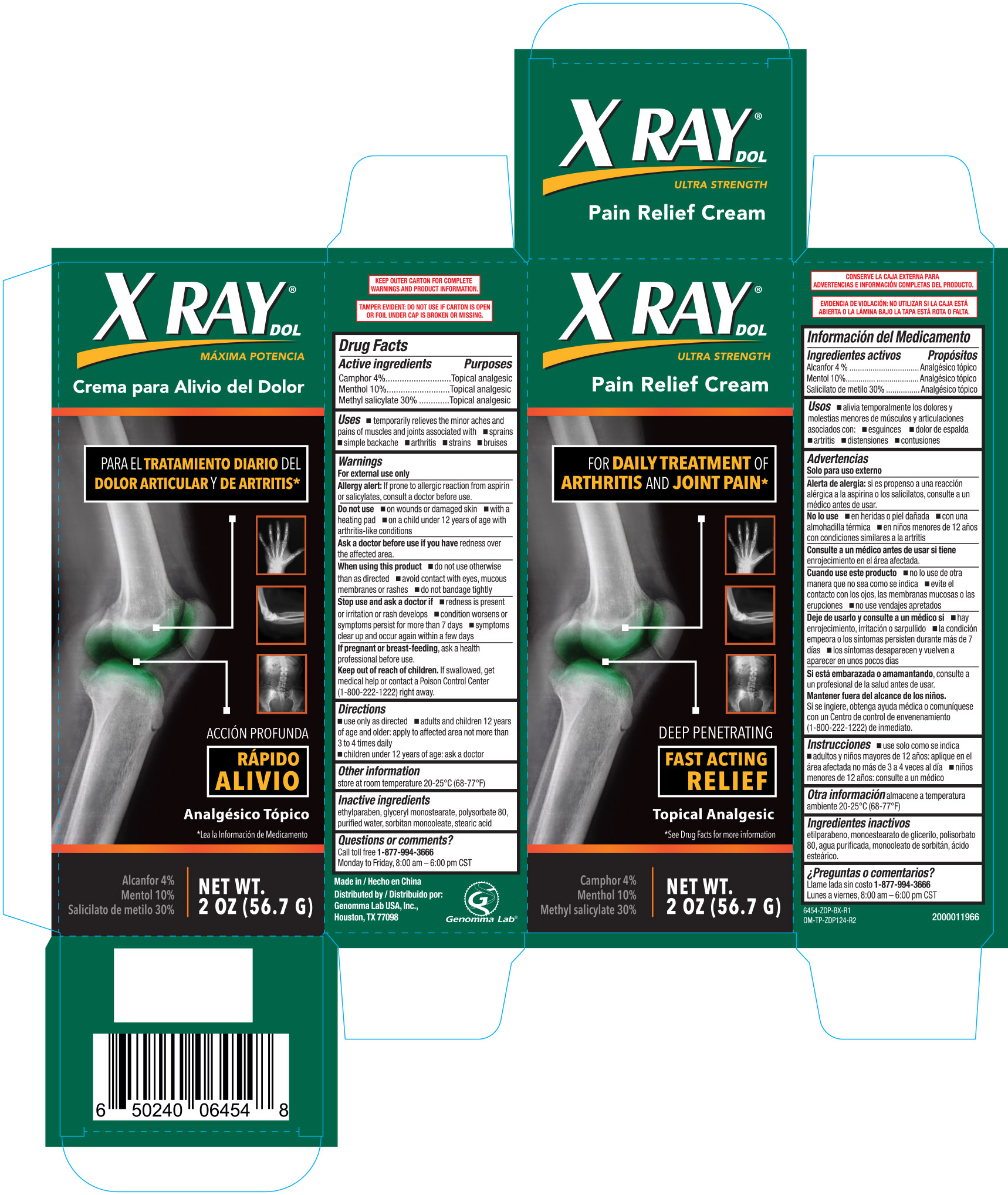 DRUG LABEL: XRay DOL
NDC: 50066-454 | Form: CREAM
Manufacturer: Genomma Lab USA, Inc.
Category: otc | Type: HUMAN OTC DRUG LABEL
Date: 20251028

ACTIVE INGREDIENTS: CAMPHOR (SYNTHETIC) 40 mg/1 g; MENTHOL 100 mg/1 g
INACTIVE INGREDIENTS: METHYL SALICYLATE 300 mg/1 g; ETHYLPARABEN; GLYCERYL MONOSTEARATE; POLYSORBATE 80; WATER; SORBITAN MONOOLEATE; STEARIC ACID

X Ray Pain Relief Cream 2oz 6454 ZDP

Active ingredients Purposes

Camphor 4%...................................Topical analgesic

Menthol 10%...................................Topical analgesic

Methyl salicylate 30%......................Topical analgesic

Uses

- temporarily relieves the minor aches and pains of muscles and joints associated with
- sprains
- simple backache
- arthritis
- strains
- bruises

Warnings

For external use only

Allergy alert: If prone to allergic reaction from aspirin or salicylates, consult a doctor before use.

Do not use

- on wounds or damaged skin
- with a heating pad
- on a child under 12 years of age with arthritis-like conditions

Ask a doctor before use if you have redness over the affected area.

When using this product

- do not use otherwise than as directed
- avoid contain with the eyes, mucous membranes or rashes
- do not bandage tightly

PREGNANCY OR BREAST FEEDING

If pregnant or breast-feeding, ask a health professional before use.

Keep out of reach of children. If swallowed, get medical help or contact a Poison Control Center (1-800-222-1222) right away

Directions

- use only as directed
- adults and children 12 years of age and older: apply to affected area not more than 3 to 4 times daily
- children under 12 years of age: ask a doctor

Other information

store at room temperature 20-25°C (68-77°F)

Inactive ingredients

ethylparaben, glyceryl monostearate, polysorbate 80, purified water, sorbitan monooleate, stearic acid

DOSAGE AND ADMINISTRATION

Distributed by

Genomma Lab USA, Inc.

Made in China